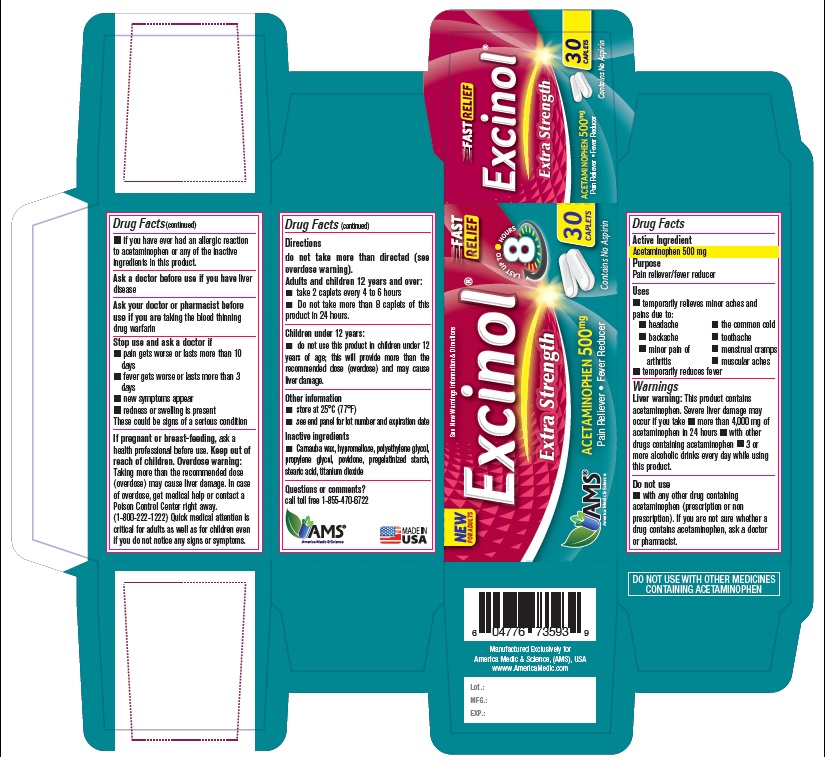 DRUG LABEL: Excinol Extra
NDC: 49638-109 | Form: TABLET, DELAYED RELEASE
Manufacturer: America Medic & Science, LLC
Category: otc | Type: HUMAN OTC DRUG LABEL
Date: 20200916

ACTIVE INGREDIENTS: ACETAMINOPHEN 500 mg/1 1
INACTIVE INGREDIENTS: CARNAUBA WAX; HYPROMELLOSE, UNSPECIFIED; POLYETHYLENE GLYCOL, UNSPECIFIED; PROPYLENE GLYCOL; POVIDONE; STARCH, CORN; STEARIC ACID; TITANIUM DIOXIDE

Excinol Extra 500 mg

Excinol Extra 500 mg

Drug Facts

Active Ingredient

Acetaminophen 500 mg

Purpose

Pain reliever/fever reducer

Uses

- temporarily relieves minor aches and pains due to:
- headache
- backache
- minor pain of arthritis
- temporarily reduces fever
- the common cold
- toothache
- menstrual cramps
- muscular aches

Warnings

Liver warning: This product contains acetaminophen. Severe liver damage may occur if you take

- more than 4,000 mg of acetaminophen in 24 hours
- with other drugs containing acetaminophen
- 3 or more alcoholic drinks every day while using this product.

Do not use

- with any other drug containing acetaminophen (prescription or non prescription). If you are not sure whether a drug contains acetaminophen, ask a doctor or pharmacist.
- if you have ever had an allergic reaction to acetaminophen or any of the inactive ingredients in this product.

Ask a doctor before use if you have liver disease

ASK DOCTOR/PHARMACIST

Ask your doctor or pharmacist before use if you are taking the blood thinning drug warfarin

Stop use and ask a doctor if

- pain gets worse or lasts more than 10 days
- fever gets worse or lasts more than 3 days
- new symptoms appear
- redness or swelling is present

These could be signs of a serious condition

PREGNANCY OR BREAST FEEDING

If pregnant or breast-feeding, ask a health professional before use.

Keep out of reach of children.

Overdose warning

Overdose warning: Taking more than the recommended dose (overdose) may cause liver damage. In case of overdose, get medical help or contact a Poison Control Center right away. (1-800-222-1222) Quick medical attention is critical for adults as well as for children even if you do not notice any signs or symptoms.

Directions

do not take more than directed (see overdose warning).

Adults and children 12 years and over:

- take 2 caplets every 4 to 6 hours
- Do not take more than 8 caplets of this product in 24 hours.

Children under 12 years:

- do not use this product in children under 12 years of age; this will provide more than the recommended dose (overdose) and may cause liver damage.

Other information

- store at 25°C (77°F)
- see end panel for lot number and expiration date

Inactive ingredients

- Carnauba wax, hypromellose, polyethylene glycol, propylene glycol, povidone, pregelatinized starch, stearic acid, titanium dioxide

Questions or comments?

call toll free 1-855-470-6722